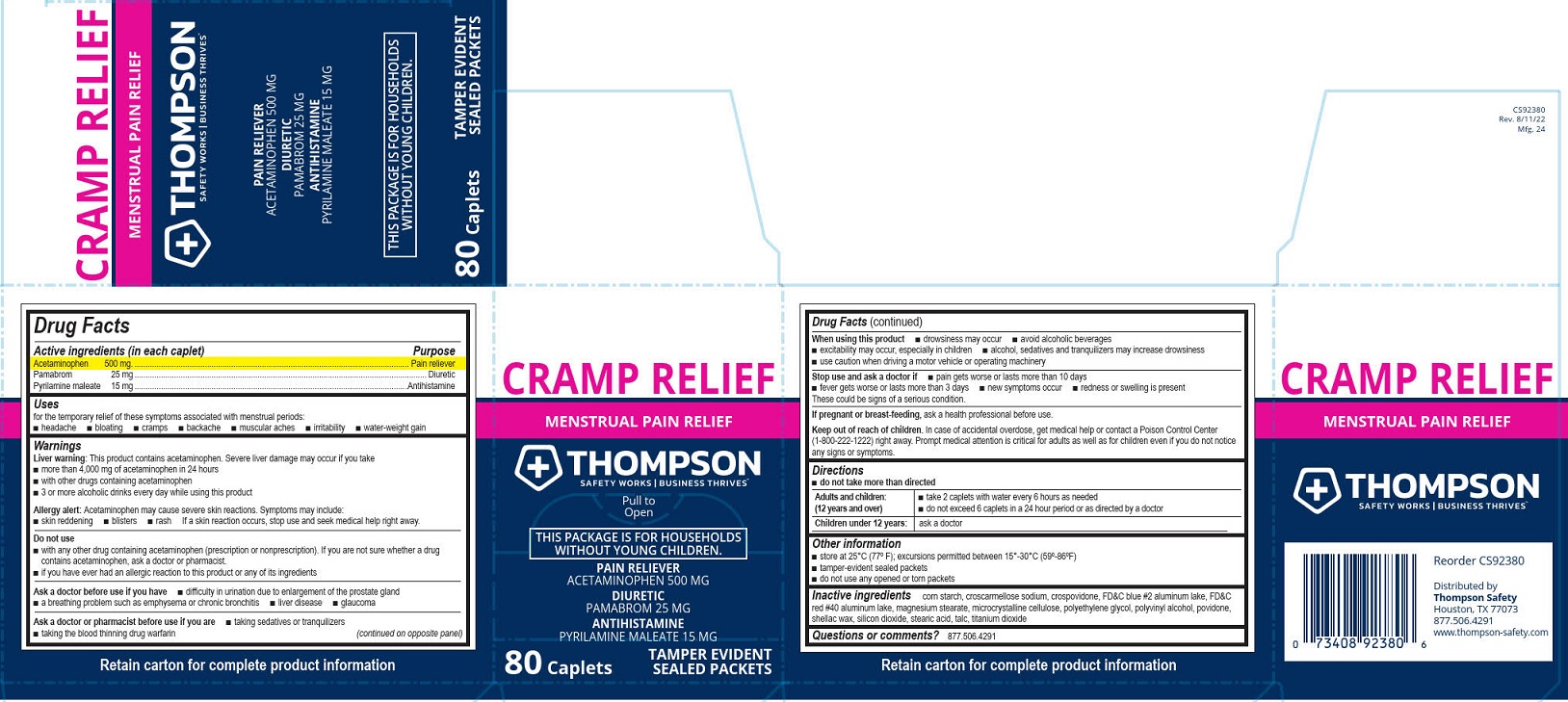 DRUG LABEL: Thompson Cramp Relief
NDC: 73408-923 | Form: TABLET, FILM COATED
Manufacturer: Thompson Safety
Category: otc | Type: HUMAN OTC DRUG LABEL
Date: 20260108

ACTIVE INGREDIENTS: ACETAMINOPHEN 500 mg/1 1; PAMABROM 25 mg/1 1; PYRILAMINE MALEATE 15 mg/1 1
INACTIVE INGREDIENTS: TITANIUM DIOXIDE; SILICON DIOXIDE; STARCH, CORN; CROSCARMELLOSE SODIUM; CROSPOVIDONE; MAGNESIUM STEARATE; SHELLAC; MICROCRYSTALLINE CELLULOSE; POLYETHYLENE GLYCOL, UNSPECIFIED; POVIDONE, UNSPECIFIED; TALC; FD&C BLUE NO. 2--ALUMINUM LAKE; FD&C RED NO. 40; POLYVINYL ALCOHOL, UNSPECIFIED; STEARIC ACID

Thompson Cramp Relief

Drug Facts

Active ingredient (in each caplet)

Acetaminophen 500 mg

Pamabrom 25 mg

Pyrilamine maleate 15 mg

Purpose

Pain reliever

Diuretic

Antihistamine

Uses

for the temporary relief of these symptoms associated with menstrual periods:

■ headache

■ bloating

■ cramps

■ backache

■ muscular aches

■ irritability

■ water-weight gain

Warnings

Liver warning: This product contains acetaminophen. Severe liver damage may occur if you take

■ more than 4,000 mg of acetaminophen in 24 hours

■ with other drugs containing acetaminophen

■ 3 or more alcoholic drinks every day while using this product

Allergy alert: Acetaminophen may cause severe skin reactions. Symptoms may include:

■ skin reddening

■ blisters

■ rash

If a skin reaction occurs, stop use and seek medical help right away.

Do not use

■ with any other drug containing acetaminophen (prescription or nonprescription). If you are not
sure whether a drug contains acetaminophen, ask a doctor or pharmacist.

■ if you have ever had an allergic reaction to this product or any of its ingredients

Ask a doctor before use if you have

■ difficulty in urination due to enlargement of the prostate gland

■ a breathing problem such as emphysema or chronic bronchitis

■ liver disease

■ glaucoma

Ask a doctor or pharmacist before use if you are

■ taking sedatives or tranquilizers

■ taking the blood thinning drug warfarin

When using this product

■ drowsiness may occur

■ avoid alcoholic beverages

■ excitability may occur, especially in children

■ alcohol, sedatives and tranquilizers may increase drowsiness

■ use caution when driving a motor vehicle or operating machinery

Stop use and ask a doctor if

■ pain gets worse or lasts more than 10 days

■ fever gets worse or lasts more than 3 days

■ new symptoms occur

■ redness or swelling is present

These could be signs of a serious condition.

PREGNANCY OR BREAST FEEDING

If pregnant or breast-feeding, ask a health professional before use.

Keep out of reach of children. In case of accidental overdose, get medical help or contact a Poison Control Center (1-800-222-1222) right away. Prompt medical attention is critical for adults as well as for children even if you do not notice any signs or symptoms.

Directions

■ do not take more than directed

Adults and children: (12 years and over)

■ take 2 caplets with water every 6 hours as needed

■ do not exceed 6 caplets in a 24 hour period or as directed by a doctor

Children under 12 years: ask a doctor

Other information

■ store at 25°C (77°F); excursions permitted between 15°-30°C (59°-86°F)

■ tamper-evident sealed packets

■ do not use any opened or torn packets

Inactive ingredients

corn starch, croscarmellose sodium, crospovidone, FD&C blue #2 aluminum lake, FD&C red #40 aluminum lake, magnesium stearate, microcrystalline cellulose, polyethylene glycol, polyvinyl alcohol, povidone, shellac wax, silicon dioxide, stearic acid, talc, titanium dioxide

Questions or comments? 877.506.4291

PACKAGE LABEL

Thompson

Cramp Relief

Menstrual Pain Relief

Pain Reliver Acetaminophen 500 mg

Diuretic Pamabrom 25 mg

Antihistamine Pyrilamine Maleate 15 mg

Safety Works | Business Thrives™

Pull to Open

This Package is for Households Without Young Children.

80 Caplets

Tamper Evident Sealed Packets